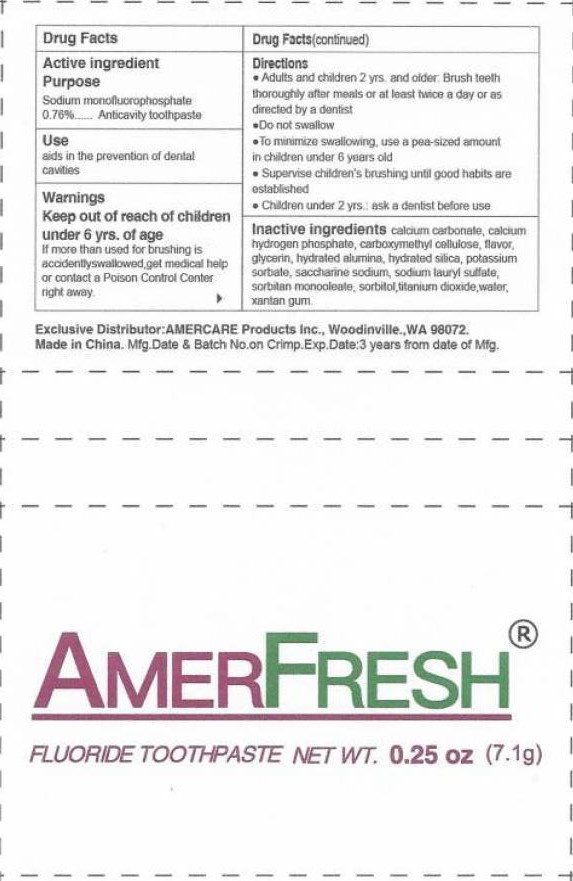 DRUG LABEL: AmerFresh Fluoride
NDC: 51460-3001 | Form: PASTE
Manufacturer: Amercare Products, Inc.
Category: otc | Type: HUMAN OTC DRUG LABEL
Date: 20160914

ACTIVE INGREDIENTS: SODIUM MONOFLUOROPHOSPHATE 0.76 g/1 g
INACTIVE INGREDIENTS: CALCIUM CARBONATE; ANHYDROUS DIBASIC CALCIUM PHOSPHATE; CARBOXYMETHYLCELLULOSE; GLYCERIN; ALUMINUM HYDROXIDE; HYDRATED SILICA; POTASSIUM SORBATE; SODIUM LAURYL SULFATE; SORBITAN MONOOLEATE; SORBITOL; TITANIUM DIOXIDE; WATER; XANTHAN GUM

AmerFresh Fluoride Toothpaste

Active Ingredient

Sodium Monofluorophosphate 0.76%

Purpose

Anticavity toothpaste

Use

Aids in the prevention of dental cavities

Warnings

If more than used for brushing is accidently swallowed, get medical help or contact a poison control center

Keep out of reach of children under 6 yrs. of age

Directions

- Adults and children 2 yrs. and older: Brush teeth throughtly after meals or at least twice a day or as directed by a dentist.
- Do not swallow
- To minimize swallowing, use a pea-sized amount in children under 6 years old.
- Supervise children's brushing until good habits are established.
- Children under 2 yrs.: ask a dentist before use.

Inactive Ingredients

SODIUM MONOFLUOROPHOSPHATE, CALCIUM CARBONATE, ANHYDROUS DIBASIC CALCIUM PHOSPHATE, CARBOXYMETHYLCELLULOSE, GLYCERIN, ALUMINUM HYDROXIDE, HYDRATED SILICA, POTASSIUM SORBATE, SODIUM LAURYL SULFATE, SORBITAN MONOOLEATE, SORBITOL, TITANIUM DIOXIDE, WATER, XANTHAN GUM.